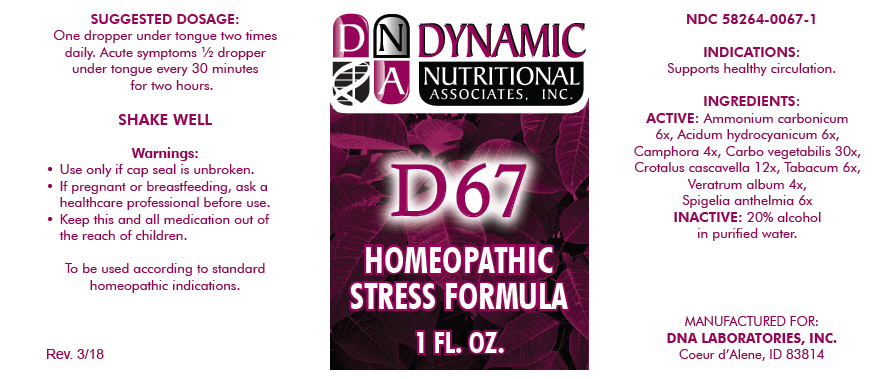 DRUG LABEL: D-67
NDC: 58264-0067 | Form: SOLUTION
Manufacturer: DNA Labs, Inc.
Category: homeopathic | Type: HUMAN OTC DRUG LABEL
Date: 20250113

ACTIVE INGREDIENTS: AMMONIUM CARBONATE 6 [hp_X]/1 mL; HYDROGEN CYANIDE 6 [hp_X]/1 mL; CAMPHOR (NATURAL) 4 [hp_X]/1 mL; ACTIVATED CHARCOAL 30 [hp_X]/1 mL; CROTALUS DURISSUS TERRIFICUS VENOM 12 [hp_X]/1 mL; TOBACCO LEAF 6 [hp_X]/1 mL; VERATRUM ALBUM ROOT 4 [hp_X]/1 mL; SPIGELIA ANTHELMIA 6 [hp_X]/1 mL
INACTIVE INGREDIENTS: ALCOHOL; WATER

D-67

NDC 58264-0067-1

INDICATIONS

PURPOSE

Supports healthy circulation.

INGREDIENTS

ACTIVE

Ammonium carbonicum 6x, Acidum hydrocyanicum 6x, Camphora 4x, Carbo vegetabilis 30x, Crotalus cascavella 12x, Tabacum 6x, Veratrum album 4x, Spigelia anthelmia 6x

INACTIVE

20% alcohol in purified water.

SUGGESTED DOSAGE

One dropper under tongue two times daily. Acute symptoms ½ dropper under tongue every 30 minutes for two hours.

STORAGE AND HANDLING

SHAKE WELL

Warnings

- Use only if cap seal is unbroken.

PREGNANCY OR BREAST FEEDING

- If pregnant or breastfeeding, ask a healthcare professional before use.

KEEP OUT OF REACH OF CHILDREN

- Keep this and all medication out of the reach of children.

To be used according to standard homeopathic indications.

PRINCIPAL DISPLAY PANEL - 1 FL. OZ. Bottle Label

DYNAMIC
NUTRITIONAL
ASSOCIATES, INC,

D 67

HOMEOPATHIC
STRESS FORMULA

1 FL. OZ.